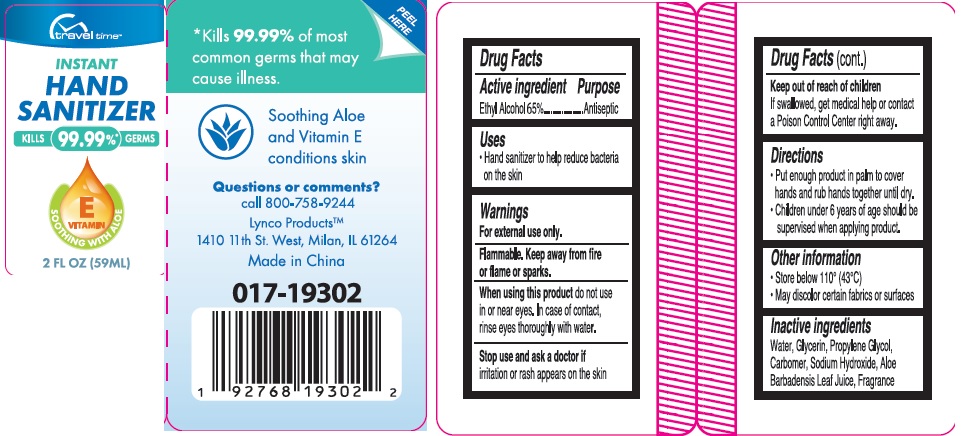 DRUG LABEL: Traveltime Instant Hand Sanitizer
NDC: 74274-007 | Form: SOLUTION
Manufacturer: Huizhou Bliss Commodity Co., Ltd
Category: otc | Type: HUMAN OTC DRUG LABEL
Date: 20200418

ACTIVE INGREDIENTS: ALCOHOL 65 mL/100 mL
INACTIVE INGREDIENTS: WATER; CARBOMER INTERPOLYMER TYPE A (ALLYL SUCROSE CROSSLINKED); GLYCERIN; PROPYLENE GLYCOL; SODIUM HYDROXIDE

Active ingredient

Ethyl Alcohol 65%

Purpose

Antiseptic

Use

Hand sanitizer to help reduce bacteria on the skin.

KEEP OUT OF REACH OF CHILDREN

if swallowed, get medical help or contact a Poison Control Center right away.

warnings:

Flamable, keep away from fire or flame or sparks.

For external use only

When using this product

- do not use in or near eyes
- If case of contact, rinse eyes thoroughly with water

Stop use and ask a doctor if

Irritation or rash appears on the skin.

Directions

- put enough product in palm to cover hands and rub hands together until dry.
- Children under 6 years of age should be supervised when applying product.

Other information:

- Store below 110° （43℃）
- May discollor certain fabrics or surfaces.

Inactive ingredients

Water, glycerin, propyene glycol, carbomer, sodium hydroxide, Aloe Barbadensis Leaf Juice, Fragrance